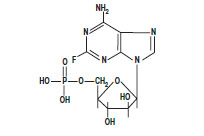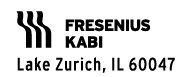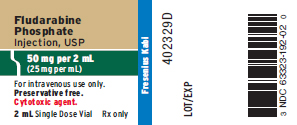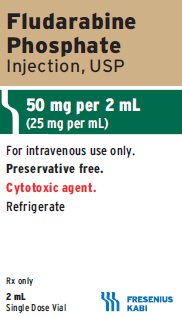 DRUG LABEL: Fludarabine

NDC: 63323-192 | Form: INJECTION, SOLUTION
Manufacturer: Fresenius Kabi USA, LLC
Category: prescription | Type: HUMAN PRESCRIPTION DRUG LABEL
Date: 20241014

ACTIVE INGREDIENTS: FLUDARABINE PHOSPHATE 25 mg/1 mL
INACTIVE INGREDIENTS: MANNITOL 25 mg/1 mL; SODIUM HYDROXIDE

Fludarabine Phosphate Injection, USP

Rx only

FOR INTRAVENOUS USE ONLY

WARNING

Fludarabine should be administered under the supervision of a qualified physician experienced in the use of antineoplastic therapy. Fludarabine can severely suppress bone marrow function. When used at high doses in dose-ranging studies in patients with acute leukemia, fludarabine was associated with severe neurologic effects, including blindness, coma, and death. This severe central nervous system toxicity occurred in 36% of patients treated with doses approximately four times greater (96 mg/m^2/day for 5 to 7 days) than the recommended dose. Similar severe central nervous system toxicity has been rarely (0.2%) reported in patients treated at doses in the range of the dose recommended for chronic lymphocytic leukemia.

Instances of life-threatening and sometimes fatal autoimmune hemolytic anemia have been reported to occur after one or more cycles of treatment with fludarabine. Patients undergoing treatment with fludarabine should be evaluated and closely monitored for hemolysis.

In a clinical investigation using fludarabine in combination with pentostatin (deoxycoformycin) for the treatment of refractory chronic lymphocytic leukemia (CLL), there was an unacceptably high incidence of fatal pulmonary toxicity. Therefore, the use of fludarabine in combination with pentostatin is not recommended.

DESCRIPTION

Fludarabine Phosphate Injection, USP contains fludarabine phosphate, a fluorinated nucleotide analog of the antiviral agent vidarabine, 9-ß-D-arabinofuranosyladenine (ara-A) that is relatively resistant to deamination by adenosine deaminase. Each mL contains 25 mg of the active ingredient fludarabine phosphate, 25 mg of mannitol, water for injection, q.s., and sodium hydroxide to adjust pH to 6.8. The pH range for the final product is 6.0 to 7.1. Fludarabine Phosphate Injection, USP is a sterile solution intended for intravenous administration.

The chemical name for fludarabine phosphate is 9 H-Purin-6-amine, 2-fluoro-9-(5- O-phosphono-ß-D-arabinofuranosyl) (2-fluoro-ara-AMP). The structure is:

C10H13FN5O7P M.W. 365.2

CLINICAL PHARMACOLOGY

Fludarabine phosphate is rapidly dephosphorylated to 2-fluoro-ara-A and then phosphorylated intracellularly by deoxycytidine kinase to the active triphosphate, 2-fluoro-ara-ATP. This metabolite appears to act by inhibiting DNA polymerase alpha, ribonucleotide reductase and DNA primase, thus inhibiting DNA synthesis. The mechanism of action of this antimetabolite is not completely characterized and may be multi-faceted.

Phase I studies in humans have demonstrated that fludarabine phosphate is rapidly converted to the active metabolite, 2-fluoro-ara-A, within minutes after intravenous infusion. Consequently, clinical pharmacology studies have focused on 2-fluoro-ara-A pharmacokinetics. After the five daily doses of 25 mg 2-fluoro-ara-AMP/m^2 to cancer patients infused over 30 minutes, 2-fluoro-ara-A concentrations show a moderate accumulation. During a 5-day treatment schedule, 2-fluoro-ara-A plasma trough levels increased by a factor of about 2. The terminal half-life of 2-fluoro-ara-A was estimated as approximately 20 hours. In vitro, plasma protein binding of fludarabine ranged between 19% and 29%.

A correlation was noted between the degree of absolute granulocyte count nadir and increased area under the concentration x time curve (AUC).

Special Populations

Pediatric Patients

Limited pharmacokinetic data for fludarabine phosphate for injection are available from a published study of children (ages 1 to 21 years) with refractory acute leukemias or solid tumors (Children’s Cancer Group Study 097). When fludarabine phosphate for injection was administered as a loading dose over 10 minutes immediately followed by a 5-day continuous infusion, steady-state conditions were reached early.

Patients with Renal Impairment

The total body clearance of the principal metabolite 2-fluoro-ara-A correlated with the creatinine clearance, indicating the importance of the renal excretion pathway for the elimination of the drug. Renal clearance represents approximately 40% of the total body clearance. Patients with moderate renal impairment (17 to 41 mL/min/m^2) receiving 20% reduced fludarabine dose had a similar exposure (AUC; 21 versus 20 nM•h/mL) compared to patients with normal renal function receiving the recommended dose. The mean total body clearance was 172 mL/min for normal and 124 mL/min for patients with moderately impaired renal function.

Clinical Studies

Two single-arm open-label studies of fludarabine have been conducted in adult patients with CLL refractory to at least one prior standard alkylating-agent containing regimen. In a study conducted by M.D. Anderson Cancer Center (MDAH), 48 patients were treated with a dose of 22 to 40 mg/m^2 daily for 5 days every 28 days. Another study conducted by the Southwest Oncology Group (SWOG) involved 31 patients treated with a dose of 15 to 25 mg/m^2 daily for 5 days every 28 days. The overall objective response rates were 48% and 32% in the MDAH and SWOG studies, respectively. The complete response rate in both studies was 13%; the partial response rate was 35% in the MDAH study and 19% in the SWOG study. These response rates were obtained using standardized response criteria developed by the National Cancer Institute CLL Working Group and were achieved in heavily pre-treated patients. The ability of fludarabine to induce a significant rate of response in refractory patients suggests minimal cross-resistance with commonly used anti-CLL agents.

The median time to response in the MDAH and SWOG studies was 7 weeks (range of 1 to 68 weeks) and 21 weeks (range of 1 to 53 weeks) respectively. The median duration of disease control was 91 weeks (MDAH) and 65 weeks (SWOG). The median survival of all refractory CLL patients treated with fludarabine was 43 weeks and 52 weeks in the MDAH and SWOG studies, respectively.

Rai stage improved to Stage II or better in 7 of 12 MDAH responders (58%) and in 5 of 7 SWOG responders (71%) who were Stage III or IV at baseline. In the combined studies, mean hemoglobin concentration improved from 9 g/dL at baseline to 11.8 g/dL at the time of response in a subgroup of anemic patients. Similarly, average platelet count improved from 63,500/mm^3 to 103,300/mm^3 at the time of response in a subgroup of patients who were thrombocytopenic at baseline.

INDICATIONS AND USAGE

Fludarabine Phosphate Injection, USP is indicated for the treatment of patients with B-cell chronic lymphocytic leukemia (CLL) who have not responded to or whose disease has progressed during treatment with at least one standard alkylating-agent containing regimen. The safety and effectiveness of Fludarabine Phosphate Injection, USP in previously untreated or non-refractory patients with CLL have not been established.

CONTRAINDICATIONS

Fludarabine Phosphate Injection, USP is contraindicated in those patients who are hypersensitive to this drug or its components.

WARNINGS: (See boxed warning)

There are clear dose-dependent toxic effects seen with fludarabine. Dose levels approximately 4 times greater (96 mg/m^2/day for 5 to 7 days) than that recommended for CLL (25 mg/m^2/day for 5 days) were associated with a syndrome characterized by delayed blindness, coma and death. Symptoms appeared from 21 to 60 days following the last dose. Thirteen of 36 patients (36%) who received fludarabine at high doses (96 mg/m^2/day for 5 to 7 days) developed this severe neurotoxicity. This syndrome has been reported rarely in patients treated with doses in the range of the recommended CLL dose of 25 mg/m^2/day for 5 days every 28 days. The effect of chronic administration of fludarabine on the central nervous system is unknown; however, patients have received the recommended dose for up to 15 courses of therapy.

Severe bone marrow suppression, notably anemia, thrombocytopenia and neutropenia, has been reported in patients treated with fludarabine. In a Phase I study in solid tumor patients, the median time to nadir counts was 13 days (range, 3 to 25 days) for granulocytes and 16 days (range, 2 to 32) for platelets. Most patients had hematologic impairment at baseline either as a result of disease or as a result of prior myelosuppressive therapy. Cumulative myelosuppression may be seen. While chemotherapy induced myelosuppression is often reversible, administration of fludarabine requires careful hematologic monitoring.

Several instances of trilineage bone marrow hypoplasia or aplasia resulting in pancytopenia, sometimes resulting in death, have been reported. The duration of clinically significant cytopenia in the reported cases has ranged from approximately 2 months to approximately 1 year. These episodes have occurred both in previously treated or untreated patients.

Instances of life-threatening and sometimes fatal autoimmune hemolytic anemia have been reported to occur after one or more cycles of treatment with fludarabine in patients with or without a previous history of autoimmune hemolytic anemia or a positive Coombs’ test and who may or may not be in remission from their disease. Steroids may or may not be effective in controlling these hemolytic episodes. The majority of patients rechallenged with fludarabine developed a recurrence in the hemolytic process. The mechanism(s) which predispose patients to the development of this complication has not been identified. Patients undergoing treatment with fludarabine should be evaluated and closely monitored for hemolysis.

Transfusion-associated graft-versus-host disease has been observed rarely after transfusion of non-irradiated blood in fludarabine treated patients. Consideration should, therefore, be given to the use of irradiated blood products in those patients requiring transfusions while undergoing treatment with fludarabine.

In a clinical investigation using fludarabine in combination with pentostatin (deoxycoformycin) for the treatment of refractory chronic lymphocytic leukemia (CLL) in adults, there was an unacceptably high incidence of fatal pulmonary toxicity. Therefore, the use of fludarabine in combination with pentostatin is not recommended.

Of the 133 CLL adult patients in the two trials, there were 29 fatalities during study. Approximately 50% of the fatalities were due to infection and 25% due to progressive disease.

Pregnancy Category D

Fludarabine may cause fetal harm when administered to a pregnant woman. Fludarabine phosphate was teratogenic in rats and in rabbits. Fludarabine phosphate was administered intravenously at doses of 0, 1, 10 or 30 mg/kg/day to pregnant rats on days 6 to 15 of gestation. At 10 and 30 mg/kg/day in rats, there was an increased incidence of various skeletal malformations. Fludarabine phosphate was administered intravenously at doses of 0, 1, 5 or 8 mg/kg/day to pregnant rabbits on days 6 to 15 of gestation. Dose-related teratogenic effects manifested by external deformities and skeletal malformations were observed in the rabbits at 5 and 8 mg/kg/day. Drug-related deaths or toxic effects on maternal and fetal weights were not observed. There are no adequate and well-controlled studies in pregnant women.

If fludarabine is used during pregnancy, or if the patient becomes pregnant while taking this drug, the patient should be apprised of the potential hazard to the fetus. Women of childbearing potential should be advised to avoid becoming pregnant.

PRECAUTIONS

General

Fludarabine is a potent antineoplastic agent with potentially significant toxic side effects. Patients undergoing therapy should be closely observed for signs of hematologic and nonhematologic toxicity. Periodic assessment of peripheral blood counts is recommended to detect the development of anemia, neutropenia and thrombocytopenia.

Tumor lysis syndrome associated with fludarabine treatment has been reported in CLL patients with large tumor burdens. Since fludarabine can induce a response as early as the first week of treatment, precautions should be taken in those patients at risk of developing this complication.

There are inadequate data on dosing of patients with renal insufficiency. Fludarabine must be administered cautiously in patients with renal insufficiency. The total body clearance of 2-fluoro-ara-A has been shown to be directly correlated with creatinine clearance. Patients with moderate impairment of renal function (creatinine clearance 30 to 70 mL/min/1.73 m^2) should have their fludarabine dose reduced by 20% and be monitored closely. Fludarabine is not recommended for patients with severely impaired renal function (creatinine clearance less than 30 mL/min/1.73 m^2).

Laboratory Tests

During treatment, the patient’s hematologic profile (particularly neutrophils and platelets) should be monitored regularly to determine the degree of hematopoietic suppression.

Drug Interactions

The use of fludarabine in combination with pentostatin is not recommended due to the risk of severe pulmonary toxicity (see WARNINGS).

Carcinogenesis

No animal carcinogenicity studies with fludarabine have been conducted.

Mutagenesis

Fludarabine phosphate was not mutagenic to bacteria (Ames test) or mammalian cells (HGRPT assay in Chinese hamster ovary cells) either in the presence or absence of metabolic activation. Fludarabine phosphate was clastogenic in vitro to Chinese hamster ovary cells (chromosome aberrations in the presence of metabolic activation) and induced sister chromatid exchanges both with and without metabolic activation. In addition, fludarabine phosphate was clastogenic in vivo (mouse micronucleus assay) but was not mutagenic to germ cells (dominant lethal test in male mice).

Impairment of Fertility

Studies in mice, rats and dogs have demonstrated dose-related adverse effects on the male reproductive system. Observations consisted of a decrease in mean testicular weights in mice and rats with a trend toward decreased testicular weights in dogs and degeneration and necrosis of spermatogenic epithelium of the testes in mice, rats and dogs. The possible adverse effects on fertility in humans have not been adequately evaluated.

Pregnancy

Teratogenic Effects: Pregnancy Category D

(See WARNINGS).

Nursing Mothers

It is not known whether this drug is excreted in human milk. Because many drugs are excreted in human milk and because of the potential for serious adverse reactions in nursing infants from fludarabine, a decision should be made to discontinue nursing or discontinue the drug, taking into account the importance of the drug for the mother.

Pediatric Use

Data submitted to the FDA was insufficient to establish efficacy in any childhood malignancy. Fludarabine was evaluated in 62 pediatric patients (median age 10, range 1 to 21) with refractory acute leukemia (45 patients) or solid tumors (17 patients). The fludarabine regimen tested for pediatric acute lymphocytic leukemia (ALL) patients was a loading bolus of 10.5 mg/m^2/day followed by a continuous infusion of 30.5 mg/m^2/day for 5 days. In 12 pediatric patients with solid tumors, dose-limiting myelosuppression was observed with a loading dose of 8 mg/m^2/day followed by a continuous infusion of 23.5 mg/m^2/day for 5 days. The maximum tolerated dose was a loading dose of 7 mg/m^2/day followed by a continuous infusion of 20 mg/m^2/day for 5 days. Treatment toxicity included bone marrow suppression. Platelet counts appeared to be more sensitive to the effects of fludarabine than hemoglobin and white blood cell counts. Other adverse events included fever, chills, asthenia, rash, nausea, vomiting, diarrhea, and infection. There were no reported occurrences of peripheral neuropathy or pulmonary hypersensitivity reaction.

ADVERSE REACTIONS

The most common adverse events include myelosuppression (neutropenia, thrombocytopenia and anemia), fever and chills, infection, and nausea and vomiting. Other commonly reported events include malaise, fatigue, anorexia, and weakness. Serious opportunistic infections have occurred in CLL patients treated with fludarabine. The most frequently reported adverse events and those reactions which are more clearly related to the drug are arranged below according to body system.

Hematopoietic Systems

Hematologic events (neutropenia, thrombocytopenia, and/or anemia) were reported in the majority of CLL patients treated with fludarabine. During fludarabine treatment of 133 patients with CLL, the absolute neutrophil count decreased to less than 500/mm^3 in 59% of patients, hemoglobin decreased from pretreatment values by at least 2 grams percent in 60%, and platelet count decreased from pretreatment values by at least 50% in 55%. Myelosuppression may be severe, cumulative, and may affect multiple cell lines. Bone marrow fibrosis occurred in one CLL patient treated with fludarabine.

Several instances of trilineage bone marrow hypoplasia or aplasia resulting in pancytopenia, sometimes resulting in death, have been reported in postmarketing surveillance. The duration of clinically significant cytopenia in the reported cases has ranged from approximately 2 months to approximately 1 year. These episodes have occurred both in previously treated or untreated patients.

Life-threatening and sometimes fatal autoimmune hemolytic anemia have been reported to occur in patients receiving fludarabine (see WARNINGS). The majority of patients rechallenged with fludarabine developed a recurrence in the hemolytic process.

Metabolic

Tumor lysis syndrome has been reported in CLL patients treated with fludarabine. This complication may include hyperuricemia, hyperphosphatemia, hypocalcemia, metabolic acidosis, hyperkalemia, hematuria, urate crystalluria, and renal failure. The onset of this syndrome may be heralded by flank pain and hematuria.

Nervous System

(See WARNINGS).

Objective weakness, agitation, confusion, visual disturbances, and coma have occurred in CLL patients treated with fludarabine at the recommended dose. Peripheral neuropathy has been observed in patients treated with fludarabine and one case of wrist-drop was reported.

Pulmonary System

Pneumonia, a frequent manifestation of infection in CLL patients, occurred in 16% and 22% of those treated with fludarabine in the MDAH and SWOG studies, respectively. Pulmonary hypersensitivity reactions to fludarabine characterized by dyspnea, cough and interstitial pulmonary infiltrate have been observed.

In postmarketing experience, cases of severe pulmonary toxicity have been observed with fludarabine use which resulted in ARDS, respiratory distress, pulmonary hemorrhage, pulmonary fibrosis, and respiratory failure. After an infectious origin has been excluded, some patients experienced symptom improvement with corticosteroids.

Gastrointestinal System

Gastrointestinal disturbances such as nausea and vomiting, anorexia, diarrhea, stomatitis, and gastrointestinal bleeding have been reported in patients treated with fludarabine.

Cardiovascular

Edema has been frequently reported. One patient developed a pericardial effusion possibly related to treatment with fludarabine. No other severe cardiovascular events were considered to be drug related.

Genitourinary System

Rare cases of hemorrhagic cystitis have been reported in patients treated with fludarabine.

Skin

Skin toxicity, consisting primarily of skin rashes, has been reported in patients treated with fludarabine.

Data in the following table are derived from the 133 patients with CLL who received fludarabine in the MDAH and SWOG studies.

PERCENT OF CLL PATIENTS REPORTING

NON-HEMATOLOGIC ADVERSE EVENTS

ADVERSE EVENTS | MDAH (N=101) | SWOG (N=32)
ANY ADVERSE EVENT | 88% | 91%
BODY AS A WHOLE | 72 | 84
FEVER | 60 | 69
CHILLS | 11 | 19
FATIGUE | 10 | 38
INFECTION | 33 | 44
PAIN | 20 | 22
MALAISE | 8 | 6
DIAPHORESIS | 1 | 13
ALOPECIA | 0 | 3
ANAPHYLAXIS | 1 | 0
HEMORRHAGE | 1 | 0
HYPERGLYCEMIA | 1 | 6
DEHYDRATION | 1 | 0
NEUROLOGICAL | 21 | 69
WEAKNESS | 9 | 65
PARESTHESIA | 4 | 12
HEADACHE | 3 | 0
VISUAL DISTURBANCE | 3 | 15
HEARING LOSS | 2 | 6
SLEEP DISORDER | 1 | 3
DEPRESSION | 1 | 0
CEREBELLAR SYNDROME | 1 | 0
IMPAIRED MENTATION | 1 | 0
PULMONARY | 35 | 69
COUGH | 10 | 44
PNEUMONIA | 16 | 22
DYSPNEA | 9 | 22
SINUSITIS | 5 | 0
PHARYNGITIS | 0 | 9
UPPER RESPIRATORY INFECTION | 2 | 16
ALLERGIC PNEUMONITIS | 0 | 6
EPISTAXIS | 1 | 0
HEMOPTYSIS | 1 | 6
BRONCHITIS | 1 | 0
HYPOXIA | 1 | 0
GASTROINTESTINAL | 46 | 63
NAUSEA/VOMITING | 36 | 31
DIARRHEA | 15 | 13
ANOREXIA | 7 | 34
STOMATITIS | 9 | 0
GI BLEEDING | 3 | 13
ESOPHAGITIS | 3 | 0
MUCOSITIS | 2 | 0
LIVER FAILURE | 1 | 0
ABNORMAL LIVER FUNCTION TEST | 1 | 3
CHOLELITHIASIS | 0 | 3
CONSTIPATION | 1 | 3
DYSPHAGIA | 1 | 0
CUTANEOUS | 17 | 18
RASH | 15 | 15
PRURITUS | 1 | 3
SEBORRHEA | 1 | 0
GENITOURINARY | 12 | 22
DYSURIA | 4 | 3
URINARY INFECTION | 2 | 15
HEMATURIA | 2 | 3
RENAL FAILURE | 1 | 0
ABNORMAL RENAL FUNCTION TEST | 1 | 0
PROTEINURIA | 1 | 0
HESITANCY | 0 | 3
CARDIOVASCULAR | 12 | 38
EDEMA | 8 | 19
ANGINA | 0 | 6
CONGESTIVE HEART FAILURE | 0 | 3
ARRHYTHMIA | 0 | 3
SUPRAVENTRICULAR TACHYCARDIA | 0 | 3
MYOCARDIAL INFARCTION | 0 | 3
DEEP VENOUS THROMBOSIS | 1 | 3
PHLEBITIS | 1 | 3
TRANSIENT ISCHEMIC ATTACK | 1 | 0
ANEURYSM | 1 | 0
CEREBROVASCULAR ACCIDENT | 0 | 3
MUSCULOSKELETAL | 7 | 16
MYALGIA | 4 | 16
OSTEOPOROSIS | 2 | 0
ARTHRALGIA | 1 | 0
TUMOR LYSIS SYNDROME | 1 | 0

More than 3,000 adult patients received fludarabine in studies of other leukemias, lymphomas, and other solid tumors. The spectrum of adverse effects reported in these studies was consistent with the data presented above.

OVERDOSAGE

High doses of Fludarabine Phosphate Injection, USP (see WARNINGS section) have been associated with an irreversible central nervous system toxicity characterized by delayed blindness, coma, and death. High doses are also associated with severe thrombocytopenia and neutropenia due to bone marrow suppression. There is no known specific antidote for Fludarabine Phosphate Injection, USP overdosage. Treatment consists of drug discontinuation and supportive therapy.

DOSAGE AND ADMINISTRATION

Usual Dose

The recommended adult dose of Fludarabine Phosphate Injection, USP is 25 mg/m^2 administered intravenously over a period of approximately 30 minutes daily for five consecutive days. Each 5 day course of treatment should commence every 28 days. Dosage may be decreased or delayed based on evidence of hematologic or nonhematologic toxicity. Physicians should consider delaying or discontinuing the drug if neurotoxicity occurs.

A number of clinical settings may predispose to increased toxicity from Fludarabine Phosphate Injection, USP. These include advanced age, renal insufficiency, and bone marrow impairment. Such patients should be monitored closely for excessive toxicity and the dose modified accordingly.

The optimal duration of treatment has not been clearly established. It is recommended that three additional cycles of Fludarabine Phosphate Injection, USP be administered following the achievement of a maximal response and then the drug should be discontinued.

Renal Insufficiency

Adult patients with moderate impairment of renal function (creatinine clearance 30 to 70 mL/min/1.73 m^2) should have a 20% dose reduction of Fludarabine Phosphate Injection, USP. Fludarabine Phosphate Injection, USP should not be administered to patients with severely impaired renal function (creatinine clearance less than 30 mL/min/1.73 m^2).

Preparation of Solutions

Fludarabine Phosphate Injection, USP: Each mL contains 25 mg fludarabine phosphate, 25 mg mannitol, water for injection, q.s.; and sodium hydroxide to adjust the pH to 6.8. The pH range for the final product is 6.0 to 7.1. In clinical studies, the product has been diluted in 100 cc or 125 cc of 5% dextrose injection USP or 0.9% sodium chloride USP.

Fludarabine Phosphate Injection, USP contains no antimicrobial preservative and thus should be used within 8 hours of initial entry. Care must be taken to assure the sterility of prepared solutions. Parenteral drug products should be inspected visually for particulate matter and discoloration prior to administration.

Handling and Disposal

Parenteral drug products should be inspected visually for particulate matter and discoloration prior to administration.

Procedures for proper handling and disposal should be considered. Consideration should be given to handling and disposal according to guidelines issued for cytotoxic drugs. Several guidelines on this subject have been published.^1–8 There is no general agreement that all of the procedures recommended in the guidelines are necessary or appropriate.

Caution should be exercised in the handling of Fludarabine Phosphate Injection, USP. The use of latex gloves and safety glasses is recommended to avoid exposure in case of breakage of the vial or other accidental spillage. If the solution contacts the skin or mucous membranes, wash thoroughly with soap and water; rinse eyes thoroughly with plain water. Avoid exposure by inhalation or by direct contact of the skin or mucous membranes.

HOW SUPPLIED

Fludarabine Phosphate Injection, USP is supplied as a clear, sterile solution. Each mL contains 25 mg of fludarabine phosphate, 25 mg of mannitol, water for injection, q.s.; and sodium hydroxide to adjust pH to 6.8. The pH range for the final product is 6.0 to 7.1.

Product No. | NDC No .
109002 | 63323-192-02 | Fludarabine Phosphate Injection, USP, 50 mg per 2 mL (25 mg per mL) in a 2 mL single dose vial, packaged individually.

REFRIGERATE AT: 2° to 8°C (36° to 46°F).

The container closure is not made with natural rubber latex.

REFERENCES

1. ONS Clinical Practice Committee. Cancer Chemotherapy Guidelines and Recommendations for Practice. Pittsburgh, Pa: Oncology Nursing Society. 1999:32-41.
2. Recommendations for the Safe Handling of Parenteral Antineoplastic Drugs. Washington, DC; Division of Safety, Clinical Center Pharmacy Department and Cancer Nursing Services, National Institute of Health; 1992. US Department of Health and Human Services, Public Health Service Publication NIH 92-2621.
3. AMA Council on Scientific Affairs. Guidelines for Handling Parenteral Antineoplastics. JAMA. 1985;253:1590-1591.
4. National Study Commission on Cytotoxic Exposure — Recommendations for Handling Cytotoxic Agents. 1987. Available from Louis P. Jeffrey, Sc.D., Chairman, National Study Commission on Cytotoxic Exposure, Massachusetts College of Pharmacy and Allied Health Sciences, 179 Longwood Avenue, Boston, MA 02115.
5. Clinical Oncological Society of Australia: Guidelines and Recommendations for Safe Handling of Antineoplastic Agents. Med J Australia. 1983;1:426-428.
6. Jones, R.B, Frank R, Mass T. Safe Handling of Chemotherapeutic Agents: A Report from the Mount Sinai Medical Center. CA Cancer Clin. 1983; 33:258-263.
7. American Society of Hospital Pharmacists. ASHP Technical Assistance Bulletin on Handling Cytotoxic and Hazardous Drugs. Am J Hosp Pharm. 1990; 47:1033-1049.
8. Controlling Occupational Exposure to Hazardous Drugs (OSHA Work-Practice Guidelines). Am J Health-Syst Pharm. 1996; 53:1669-1685.

www.fresenius-kabi.us

451085C

Revised: September 2016

PACKAGE LABEL

PACKAGE LABEL - PRINCIPAL DISPLAY - Fludarabine 2 mL Single Dose Vial Label

Fludarabine Phosphate Injection, USP
50 mg per 2 mL
(25 mg per mL)
For intravenous use only.
Preservative free.
Cytotoxic agent.
2 mL Single Dose Vial Rx only

PACKAGE LABEL - PRINCIPAL DISPLAY - Fludarabine 2 mL Single Dose Vial Carton Panel

Fludarabine Phosphate Injection, USP
50 mg per 2 mL
(25 mg per mL)
For intravenous use only.
Preservative free.
Cytotoxic agent.
Refrigerate
Rx only
2 mL
Single Dose Vial